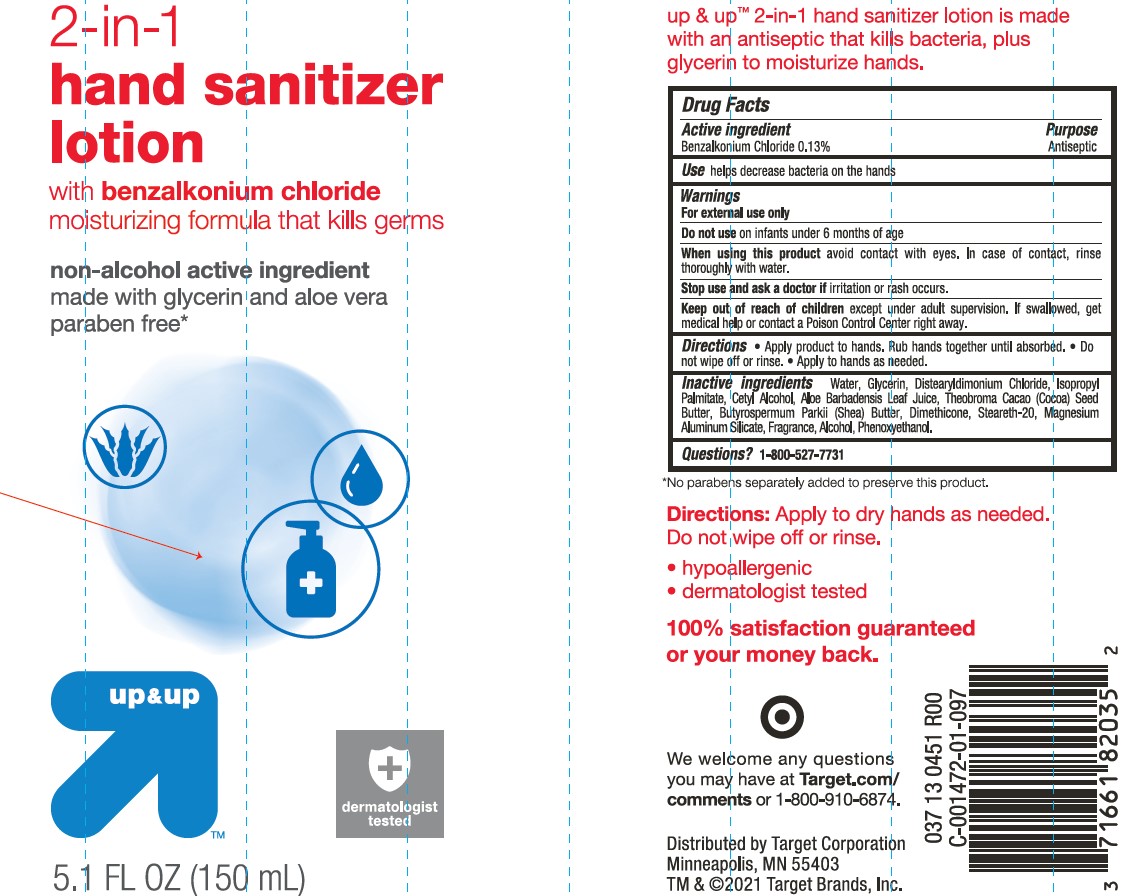 DRUG LABEL: Target Up and Up 2-in-1 Hand Sanitizer
NDC: 11673-147 | Form: LOTION
Manufacturer: TARGET CORPORATION
Category: otc | Type: HUMAN OTC DRUG LABEL
Date: 20241014

ACTIVE INGREDIENTS: BENZALKONIUM CHLORIDE 1.3 mg/1 mL
INACTIVE INGREDIENTS: STEARETH-20; SHEA BUTTER; GLYCERIN; WATER; ALOE VERA LEAF; COCOA BUTTER; PHENOXYETHANOL; MAGNESIUM ALUMINUM SILICATE; DISTEARYLDIMONIUM CHLORIDE; CETYL ALCOHOL; ALCOHOL; DIMETHICONE; ISOPROPYL PALMITATE

Target Up & Up 2-in-1 Hand Sanitizer Lotion

Active Ingredient

Benzalkonium Chloride 0.13%

Purpose

Antiseptic

Use

helps decrease bacteria on the hands

Warnings

For external use only

Do not use

on infants under 6 months of age

When using this product

avoid contact with eyes. In case of contact, rinse thoroughly with water.

Stop use and ask a doctor if

irritation or rash occurs.

Keep out of reach of children

except under adult supervision. If swallowed, get medical help or contact a Poison Control right away.

Directions

- Apply product to hands. Rub hands together until absorbed.
- Do not wipe off or rinse.
- Apply to hands as needed.

Inactive ingredients

Water, Glycerin, Distearyldimonim Chloride, Isopropyl Palmitate, Aloe Barbadensis Leaf Juice, Theobroma Cacao (Cocoa) Seed Butter, Butyrospermum Parkii (Shea) Btter, Dimethicone, Steareth-20, Magnesium Silicate, Fragrance, Alcohol, Phenoxyethanol.